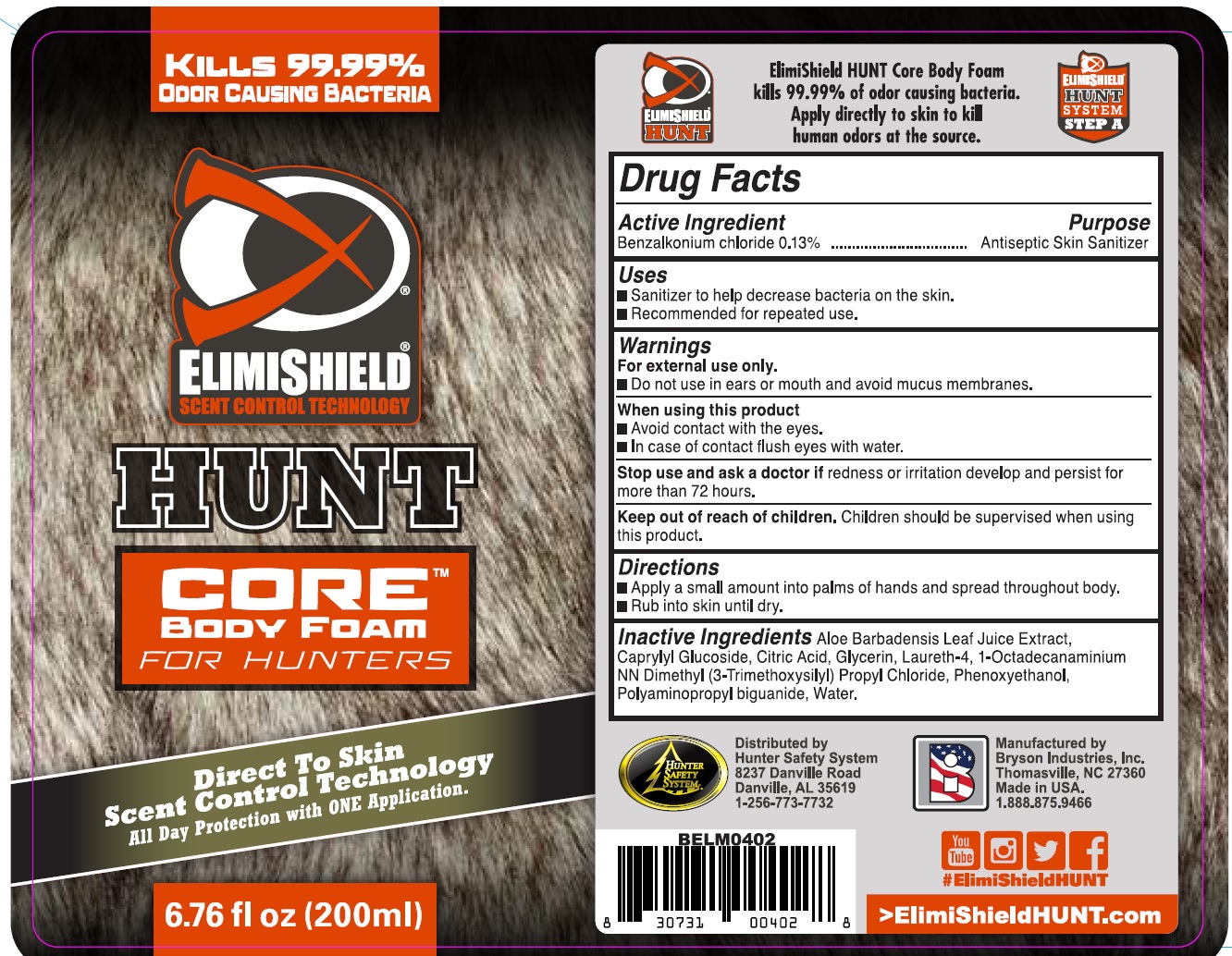 DRUG LABEL: ElimiShield Hunt Core Body Foam for Hunters
NDC: 71853-010 | Form: AEROSOL, FOAM
Manufacturer: Bryson Industries, Inc.
Category: otc | Type: HUMAN OTC DRUG LABEL
Date: 20231109

ACTIVE INGREDIENTS: BENZALKONIUM CHLORIDE 1.3 mg/1 mL
INACTIVE INGREDIENTS: ALOE VERA LEAF; CAPRYLYL GLUCOSIDE; CITRIC ACID MONOHYDRATE; GLYCERIN; LAURETH-4; PHENOXYETHANOL; POLYAMINOPROPYL BIGUANIDE; WATER

ElimiShield Hunt Core Body Foam for Hunters

Active Ingredient

Benzalkonium chloride 0.13%

Purpose

Antiseptic Skin Sanitizer

Uses

- Sanitizer to help decrease bacteria on the skin.
- Recommended for repeated use.

Warnings

For external use only.

- Do not use in ears or mouth and avoid mucus membranes.

When using this product

- Avoid contact with the eyes.
- In case of contact flush eyes with water.

Stop use and ask a doctor if

redness or iirtation develops and persist for more than 72 hours.

Keep out of reach of children.

Children should be supervised when using this product.

Directions

- Apply a small amount into palms of hands and spread throughout body.
- Rub into skin until dry.

Inactive Ingredients

Aloe Barbadensis Leaf Juice extract.Caprylyl Glucoside, Citric Acid, Glycerin, Laureth-4, 1-Octadecanaminium NN Dimethyl (3-Trimethoxysilyl) Propyl Chloride, Phenoxyethanol, Polyaminopropyl biguanide, Water.